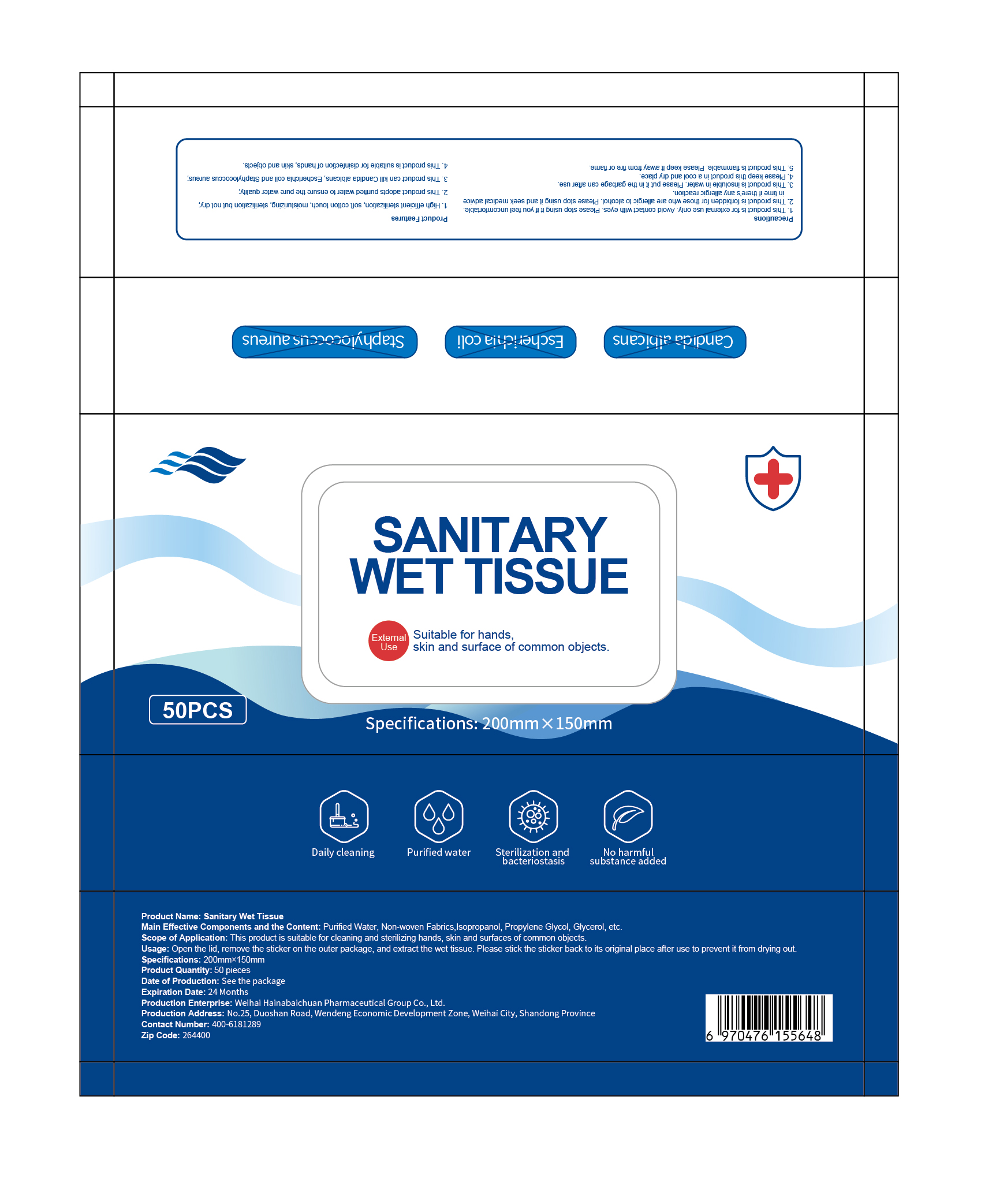 DRUG LABEL: SANITARY WET TISSUE
NDC: 96386-002 | Form: CLOTH
Manufacturer: WEIHAI HAI NA BAI CHUAN PHARMACEUTICAL GROUP
Category: otc | Type: HUMAN OTC DRUG LABEL
Date: 20200831

ACTIVE INGREDIENTS: ISOPROPYL ALCOHOL 150 mL/50 1
INACTIVE INGREDIENTS: GLYCERIN; PROPYLENE GLYCOL; WATER

Active Ingredient(s)

Isopropanol

Purpose

suitable for hands,skin and surface of common objects

Use

this product is suitable for cleaning and sterilizing hands,skin and surface of common objects.

Warnings

For external use only. Flammable. Keep away from heat or flame

Do not use

- in children less than 2 months of age
- on open skin wounds

WHEN USING

this prodcut is for extermal use only.avoid contact with eyes.please stop using it if you feel uncomfortable

STOP USE

this product is forbidden for those who are allergic to alcohol,please stop using it and seek medical advice in time if there's any allergic reaction

Keep out of reach of children. If swallowed, get medical help or contact a Poison Control Center right away.

usage

open the lid,remove the sticker on the outer package,and extract the wet tissue,please stick the sticker back to its original place after use to prevent it from drying out

Other information

- Store between 15-30C (59-86F)
- Avoid freezing and excessive heat above 40C (104F)

Inactive ingredients

glycerin, propylene glycol, purified water